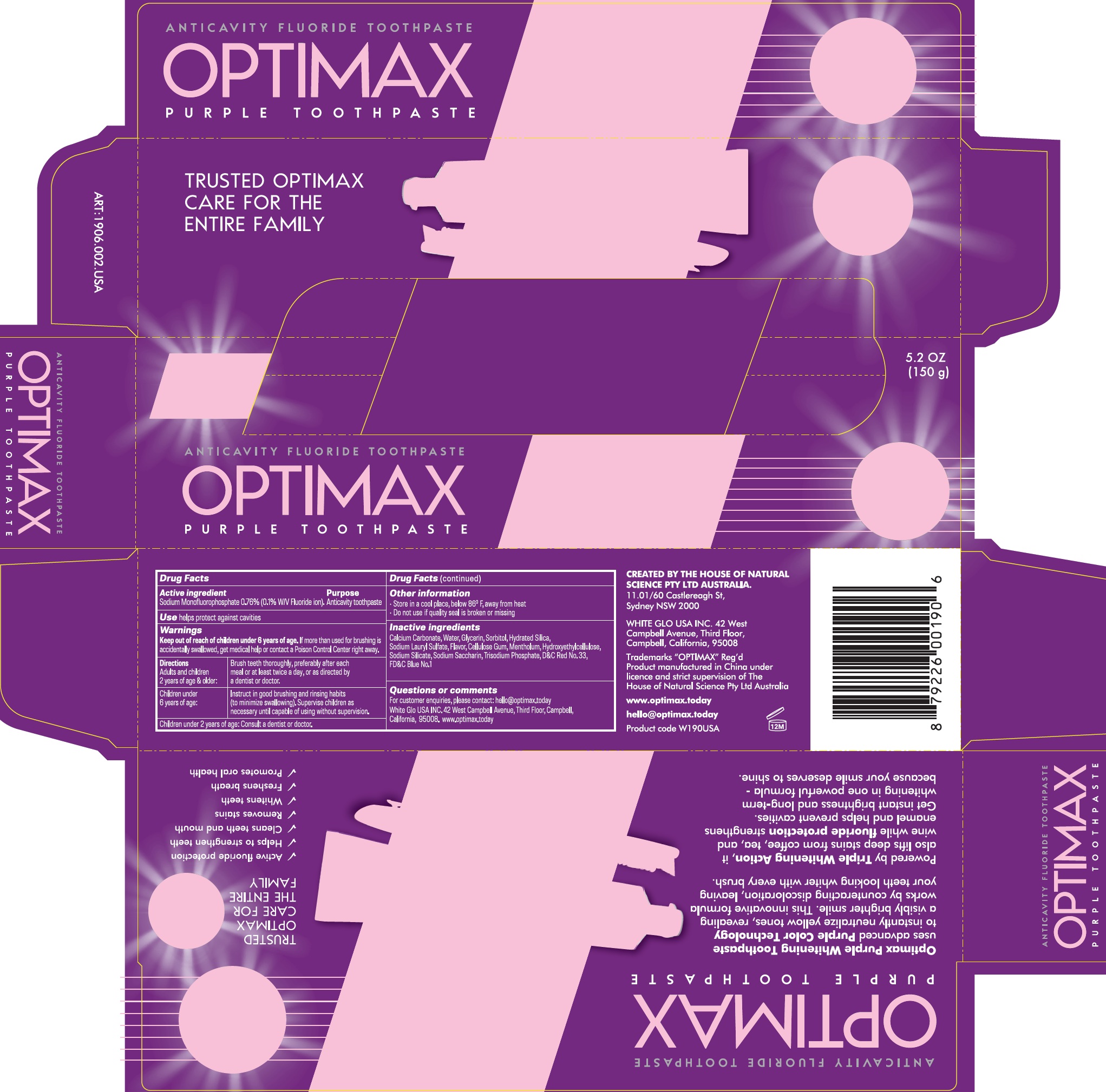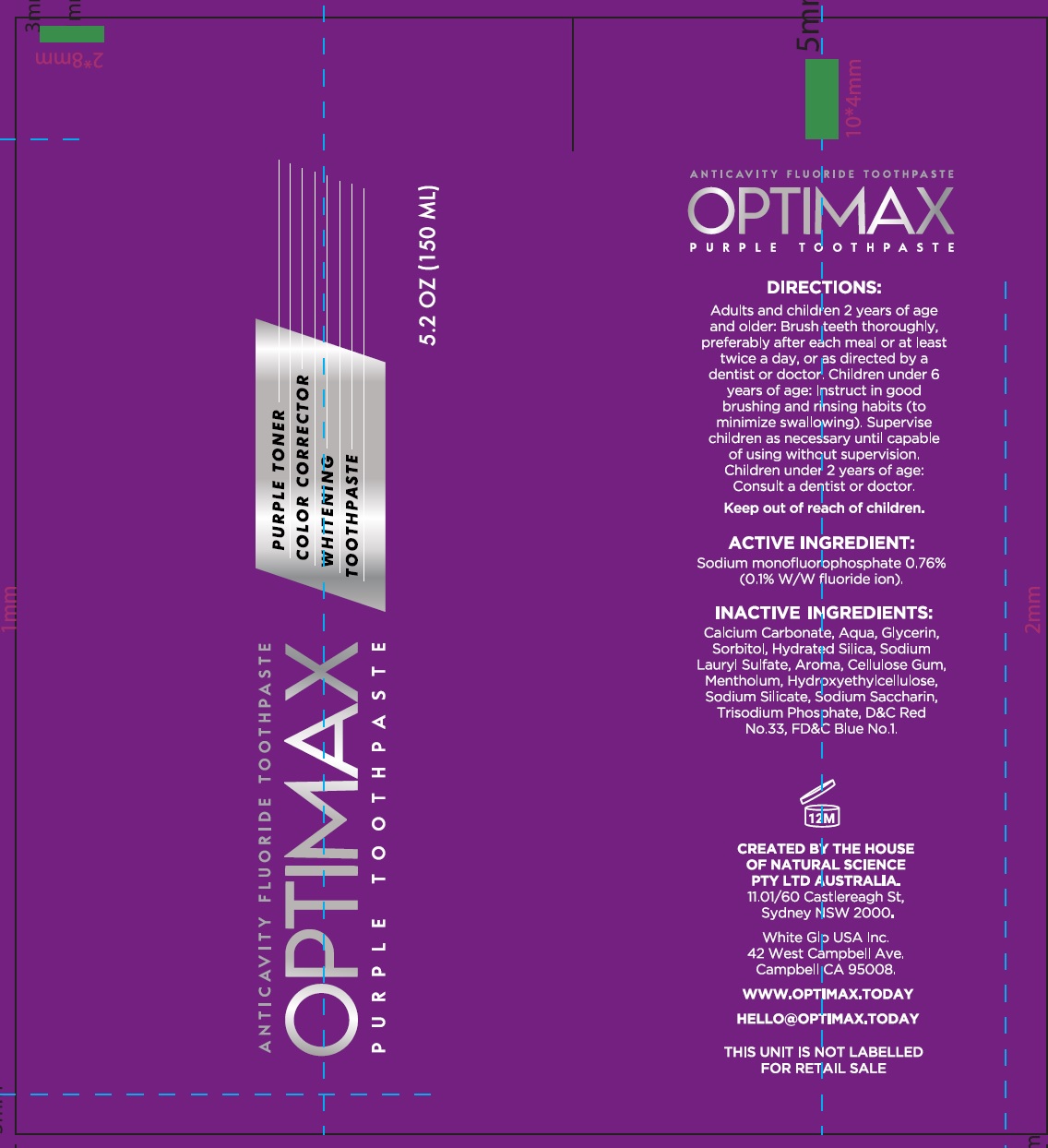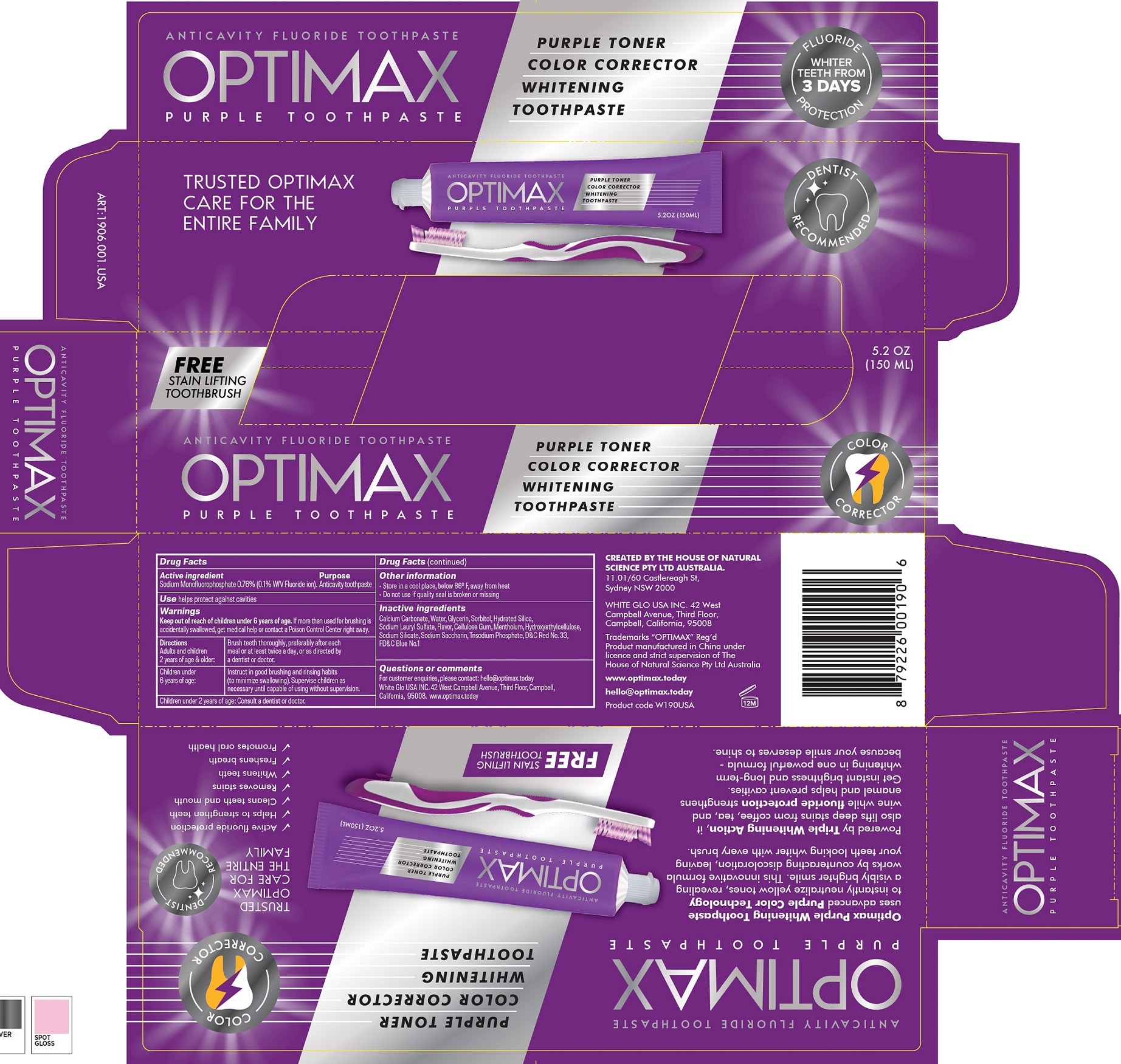 DRUG LABEL: Optimax Purple Anticavity Fluoride
NDC: 73656-039 | Form: KIT | Route: DENTAL
Manufacturer: WHITE GLO USA INC
Category: otc | Type: HUMAN OTC DRUG LABEL
Date: 20251002

ACTIVE INGREDIENTS: SODIUM MONOFLUOROPHOSPHATE 7.6 mg/1 g
INACTIVE INGREDIENTS: CALCIUM CARBONATE; WATER; GLYCERIN; SORBITOL; HYDRATED SILICA; SODIUM LAURYL SULFATE; CARBOXYMETHYLCELLULOSE SODIUM, UNSPECIFIED; MENTHOL, UNSPECIFIED FORM; HYDROXYETHYL CELLULOSE, UNSPECIFIED; SODIUM SILICATE; SACCHARIN SODIUM; D&C RED NO. 33; FD&C BLUE NO. 1

Optimax Purple Anticavity Fluoride Toothpaste

Active ingredient

Sodium Monofluorophosphate 0.76% (0.1% W/V fluoride ion).

Purpose

Anticavity toothpaste

Use

helps protect against cavities

Warnings

Keep out of reach of children under 6 years of age.

If more than used for brushing is accidentally swallowed, get medical help or contact a Poison Control Center right away.

Directions

Adults and children 2 years of age & older: | Brush teeth thoroughly, preferably after each meal or at least twice a day, or as directed by a dentist or doctor.
Children under 6 years of age: | Instruct in good brushing and rinsing habits (to minimize swallowing). Supervise children as necessary until capable of using without supervision.

Children under 2 years of age: Consult a dentist or doctor.

Other information

- Store in a cool place, below 86° F, away from heat
- Do not use if quality seal is broken or missing

Inactive ingredients

Calcium Carbonate, Water, Glycerin, Sorbitol, Hydrated Silica, Sodium Lauryl Sulfate, Flavor, Cellulose Gum, Mentholum, Hydroxyethylcellulose, Sodium Silicate, Sodium Saccharin, Trisodium Phosphate, D&C Red No.33, FD&C Blue No.1

Questions or comments

For customer enquiries, please contact: hello@optimax.today
White Glo USA INC.42 West Campbell Avenue, Third Floor, Campbell, California, 95008. www.optimax.today